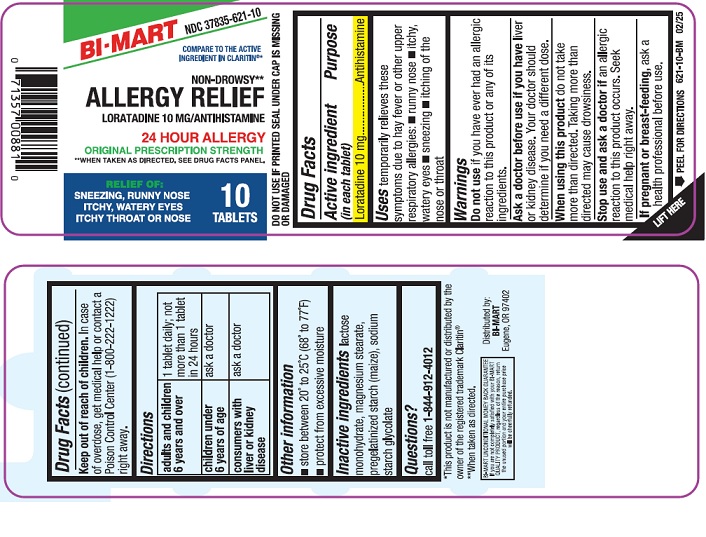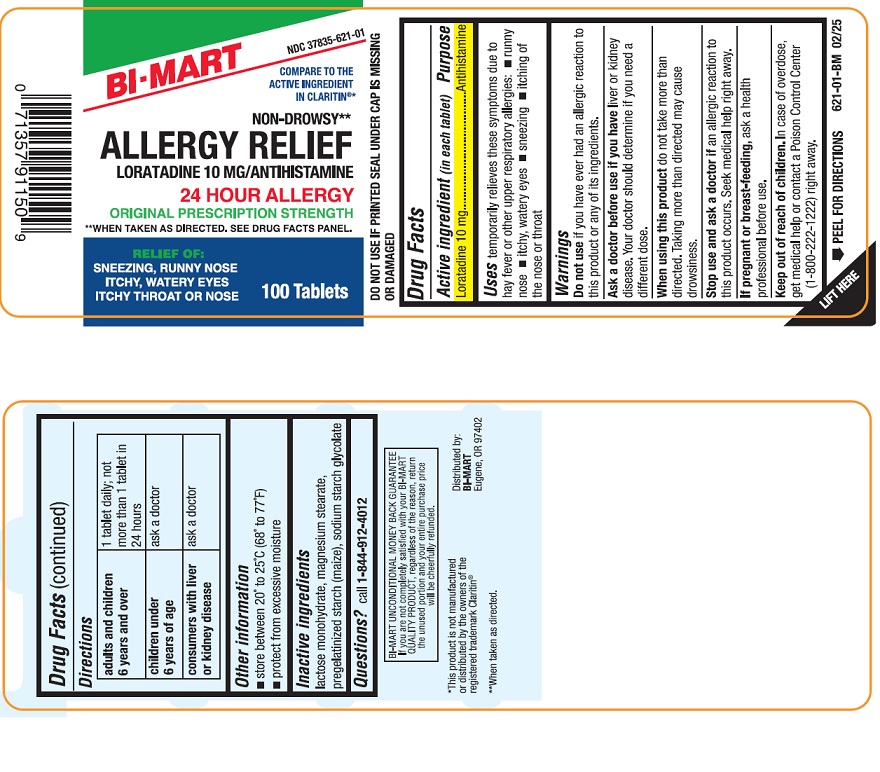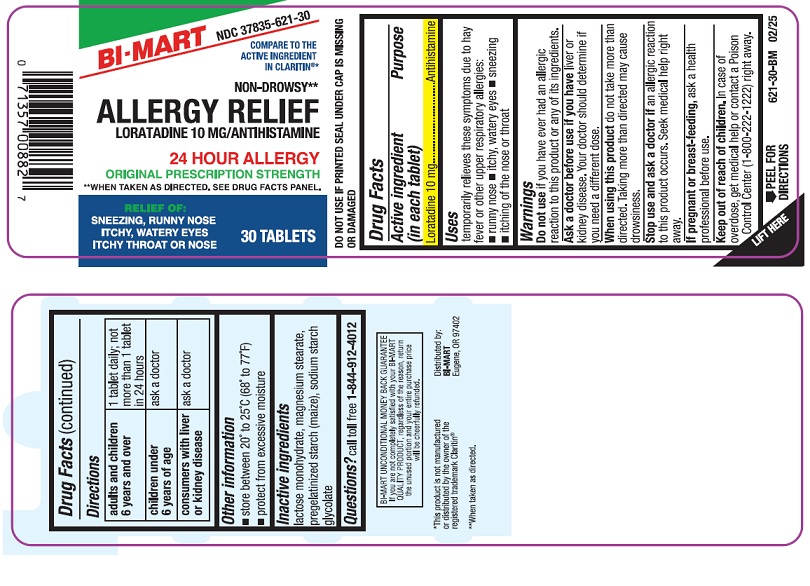 DRUG LABEL: Loratadine
NDC: 37835-621 | Form: TABLET
Manufacturer: Bi-Mart
Category: otc | Type: HUMAN OTC DRUG LABEL
Date: 20250411

ACTIVE INGREDIENTS: LORATADINE 10 mg/1 1
INACTIVE INGREDIENTS: LACTOSE MONOHYDRATE; STARCH, CORN; MAGNESIUM STEARATE; SODIUM STARCH GLYCOLATE TYPE A POTATO

Loratadine Tablets, 10 mg

Active ingredient (in each tablet)

Loratadine 10 mg

Purpose

Antihistamine

Uses

temporarily relieves these symptoms due to hay fever or other upper respiratory allergies:

- runny nose
- itchy, watery eyes
- sneezing
- itching of the nose or throat

Warnings

DO NOT USE

Do not useif you have ever had an allergic reaction to this product or any of its ingredients.

Ask a doctor before use ifyou haveliver or kidney disease. Your doctor should determine if you need a different dose.

WHEN USING

When using this productdo not take more than directed. Taking more than directed may cause drowsiness.

Stop use and ask doctor ifan allergic reaction to this product occurs. Seek medical help right away.

PREGNANCY OR BREAST FEEDING

If pregnant or breast-feeding,ask a health professional before use.

Keep out of reach of children. In case of overdose, get medical help or contact a Poison Control Center (1-800-222-1222) right away.

Directions

adults and children 6 years and over | 1 tablet daily; not more than 1 tablet in 24 hours
children under 6 years of age | ask a doctor
consumers with liver or kidney disease | ask a doctor

Other information

- store between 20° and 25°C (68° and 77°F)
- protect from excessive moisture
- DO NOT USE IF PRINTED SEAL UNDER CAP IS MISSING OR DAMAGED.

Inactive ingredients

lactose monohydrate, magnesium stearate, pregelatinized starch (maize), sodium starch glycolate

Questions?

call toll free 1-844-912-4012

Distributed by:

BI-MART

Eugene, OR 97402

PRINCIPAL DISPLAY PANEL-10 Tablets

NDC 37835-621-10

Compare to the Active Ingredient in Claritin®*

Non-Drowsy**

Allergy Relief

Loratadine 10 mg/Antihistamine

24 Hour Allergy

Relief of:

- Sneezing, runny nose
- Itchy, watery eyes
- Itchy throat or nose

Original Prescription Strength

**When Taken as Directed. See Drug Facts Panel.

10 Tablets

*This product is not manufactured or distributed by the owner of the registered trademark Claritin®

PRINCIPAL DISPLAY PANEL-30 Tablets

NDC 37835-621-30

Compare to the Active Ingredient in Claritin®*

Non-Drowsy**

Allergy Relief

Loratadine 10 mg/Antihistamine

24 Hour Allergy

Relief of:

- Sneezing, runny nose
- Itchy, watery eyes
- Itchy throat or nose

Original Prescription Strength

**When Taken as Directed. See Drug Facts Panel.

30 Tablets

*This product is not manufactured or distributed by the owner of the registered trademark Claritin®

PRINCIPAL DISPLAY PANEL-100 Tablets

NDC 37835-621-01

Compare to the Active Ingredient in Claritin®*

Non-Drowsy**

Allergy Relief

Loratadine 10 mg/Antihistamine

24 Hour Allergy

Relief of:

- Sneezing, runny nose
- Itchy, watery eyes
- Itchy throat or nose

Original Prescription Strength

**When Taken as Directed. See Drug Facts Panel.

100 Tablets

*This product is not manufactured or distributed by the owner of the registered trademark Claritin®